DRUG LABEL: Vitamin A and D
NDC: 57896-110 | Form: OINTMENT
Manufacturer: Geri-care Pharmaceutials Corp
Category: otc | Type: HUMAN OTC DRUG LABEL
Date: 20241217

ACTIVE INGREDIENTS: PETROLATUM 76 g/100 g
INACTIVE INGREDIENTS: MINERAL OIL; VITAMIN A PALMITATE; CHOLECALCIFEROL; MICROCRYSTALLINE WAX; PARAFFIN

Geri-Care Vitamin A & D Ointment

Active Ingredient

White Petrolatum 76%

Purpose

Skin Protectant

Uses

Temporarily protects minor cuts, scrapes and burns.

Temporarily protects and helps chapped lips and cracked skin

Helps protect lips from drying effects of wind and cold weather

Stop use and ask a doctor

Condition worsens

Symptoms last more than 7 days or clear up and occur again with a few days

Keep out of reach of children

If swallowed, get medical help or contact a Poison Control Center immediately

When using this product

Do not get in eyes

Do Not Use

- On deep or puncture wounds
- Animal Bites
- Serious Burns

Directions

Apply as needed

Inactive ingredients

mineral oil, vitamin A Palmitate, vitamin D3, Microcrystalline Wax, Paraffin

Distributed By

Geri-care Pharmaceuticals Corp

1295 Towbin Avenue

Lakewood, NJ 08701

Warnings

For external use only

Questions

Call: 1-800-540-3765

Other Information

Store at controlled room temperature 68º-77ºF (20º-25ºC)

Tamper evident, do not use if packet is torn, cut or opened

Avoid excessive heat and humidity